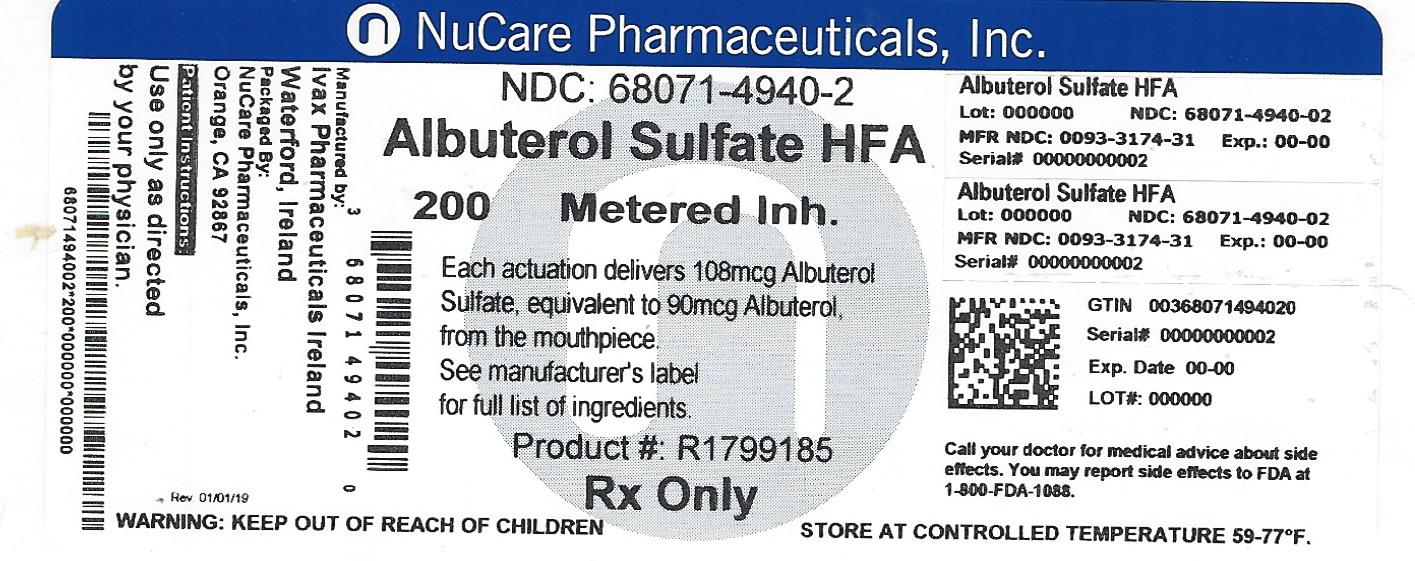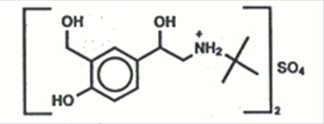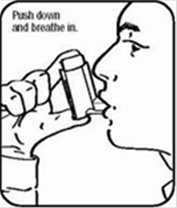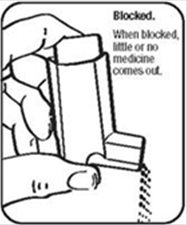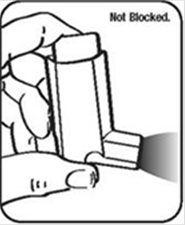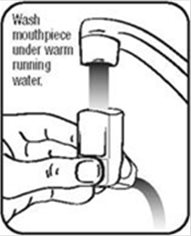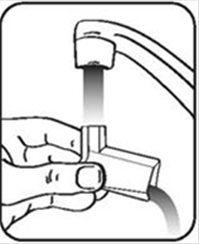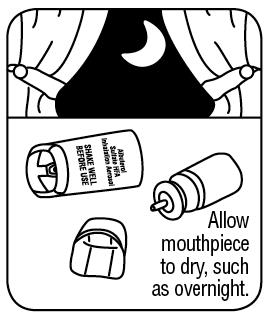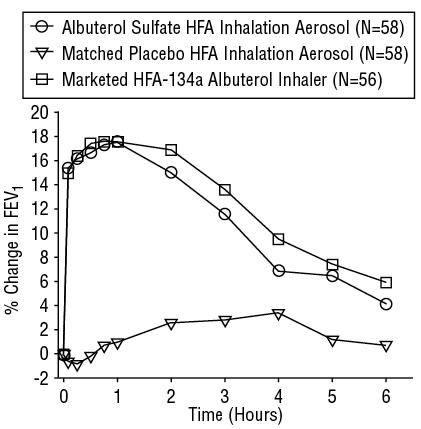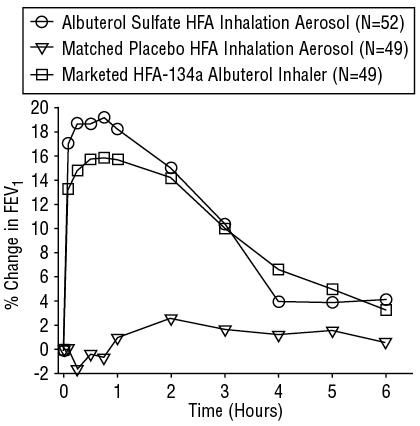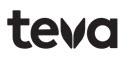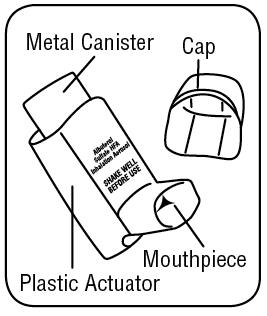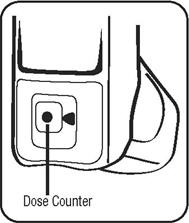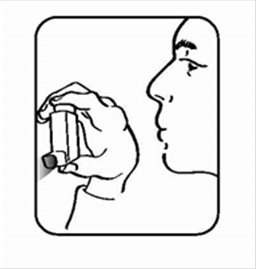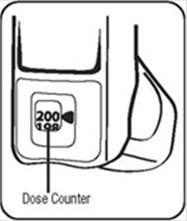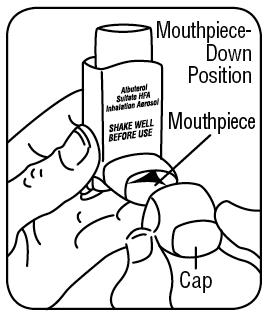 DRUG LABEL: Albuterol Sulfate
NDC: 68071-4940 | Form: AEROSOL, METERED
Manufacturer: NuCare Pharmaceuticals,Inc.
Category: prescription | Type: HUMAN PRESCRIPTION DRUG LABEL
Date: 20240618

ACTIVE INGREDIENTS: ALBUTEROL SULFATE 90 ug/1 1
INACTIVE INGREDIENTS: NORFLURANE; ALCOHOL

HIGHLIGHTS OF PRESCRIBING INFORMATION

These highlights do not include all the information needed to use Albuterol Sulfate HFA safely and effectively. See full prescribing information for Albuterol Sulfate HFA Inhalation Aerosol
ALBUTEROL SULFATE HFA INHALATION AEROSOL
Initial U.S. Approval: 1981

1 INDICATIONS AND USAGE

Albuterol Sulfate HFA Inhalation Aerosol is a beta2-adrenergic agonist indicated for:

- Treatment or prevention of bronchospasm in patients 4 years of age and older with reversible obstructive airway disease. (1.1)
- Prevention of exercise-induced bronchospasm in patients 4 years of age and older. (1.2)

2 DOSAGE AND ADMINISTRATION

For oral inhalation only

- Treatment or prevention of bronchospasm in adults and children 4 years of age and older: 2 inhalations every 4 to 6 hours. In some patients, one inhalation every 4 hours may be sufficient. (2.1)
- Prevention of exercise-induced bronchospasm in adults and children 4 years of age and older: 2 inhalations 15 to 30 minutes before exercise. (2.2)
- Priming information: Prime Albuterol Sulfate HFA before using for the first time, or when the inhaler has not been used for more than 2 weeks. To prime Albuterol Sulfate HFA, release 3 sprays into the air away from the face. Shake well before each spray. (2.3)
- Cleaning information: At least once a week, wash the actuator with warm water, shake off excess, and air dry thoroughly. (2.3)
- Albuterol Sulfate HFA inhaler should be discarded when the dose counter displays 0 or after the expiration date on the product, whichever comes first. (2.3)

3 DOSAGE FORMS & STRENGTHS

Inhalation Aerosol: Each actuation delivers 108 mcg of albuterol sulfate from the actuator mouthpiece (equivalent to 90 mcg of albuterol base). Supplied in 8.5-g canister containing 200 actuations. (3)

4 CONTRAINDICATIONS

Hypersensitivity to albuterol and any other Albuterol Sulfate HFA Inhalation Aerosol Components. (4)

5 WARNINGS & PRECAUTIONS

- Life-threatening paradoxical bronchospasm may occur. Discontinue Albuterol Sulfate HFA immediately and treat with alternative therapy. (5.1)
- Need for more doses of Albuterol Sulfate HFA than usual may be a sign of deterioration of asthma and requires reevaluation of treatment. (5.2)
- Albuterol Sulfate HFA is not a substitute for corticosteroids. (5.3)
- Cardiovascular effects may occur. Use with caution in patients sensitive to sympathomimetic drugs and patients with cardiovascular or convulsive disorders. (5.4, 5.7)
- Excessive use may be fatal. Do not exceed recommended dose. (5.5)
- Immediate hypersensitivity reactions may occur. Discontinue Albuterol Sulfate HFA immediately. (5.6)
- Hypokalemia and changes in blood glucose may occur. (5.7, 5.8)

6 ADVERSE REACTIONS

Most common adverse reactions (≥3.0% and >placebo) are headache, tachycardia, pain, dizziness, pharyngitis, and rhinitis. (6.1)

To report SUSPECTED ADVERSE REACTIONS, contact Teva Respiratory, LLC at 1-888-482-9522 or FDA at 1-800-FDA-1088 or www.fda.gov/medwatch.

7 DRUG INTERACTIONS

- Other short-acting sympathomimetic aerosol bronchodilators and adrenergic drugs: May potentiate effect. (7)
- Beta-blockers: May decrease effectiveness of Albuterol Sulfate HFA and produce severe bronchospasm. Patients with asthma should not normally be treated with beta-blockers. (7.1)
- Diuretics, or non-potassium sparing diuretics: May potentiate hypokalemia or ECG changes. Consider monitoring potassium levels. (7.2)
- Digoxin: May decrease serum digoxin levels. Consider monitoring digoxin levels. (7.3)
- Monoamine oxidase (MAO) inhibitors and tricyclic antidepressants: May potentiate effect of albuterol on the cardiovascular system. Consider alternative therapy in patients taking MAOs or tricyclic antidepressants. (7.4)

FULL PRESCRIBING INFORMATION

1 INDICATIONS AND USAGE

1.1 Bronchospasm

Albuterol Sulfate HFA Inhalation Aerosol is indicated for the treatment or prevention of bronchospasm in patients 4 years of age and older with reversible obstructive airway disease.

1.2 Exercise-Induced Bronchospasm

Albuterol Sulfate HFA Inhalation Aerosol is indicated for the prevention of exercise-induced bronchospasm in patients 4 years of age and older.

2 DOSAGE AND ADMINISTRATION

2.1 Bronchospasm

For treatment of acute episodes of bronchospasm or prevention of symptoms associated with bronchospasm, the usual dosage for adults and children 4 years and older is two inhalations repeated every 4 to 6 hours. More frequent administration or a larger number of inhalations is not recommended. In some patients, one inhalation every 4 hours may be sufficient.

2.2 Exercise-Induced Bronchospasm

The usual dosage for adults and children 4 years of age or older is two inhalations 15 to 30 minutes before exercise.

2.3 Administration Information

Administer Albuterol Sulfate HFA by oral inhalation only. Shake well before each spray. To maintain proper use of this product and to prevent medication build-up and blockage, it is important to follow the cleaning directions carefully.

Priming: Prime the inhaler before using for the first time and in cases where the inhaler has not been used for more than 2 weeks by releasing three sprays into the air, away from the face.

Cleaning: As with all HFA-containing albuterol inhalers, to maintain proper use of this product and to prevent medication build-up and blockage, it is important to clean the plastic mouthpiece regularly. The inhaler may cease to deliver medication if the plastic actuator mouthpiece is not properly cleaned and dried. To clean: Wash the plastic mouthpiece with warm running water for 30 seconds, shake off excess water, and air dry thoroughly at least once a week . If the patient has more than one Albuterol Sulfate HFA inhaler, the patient should wash each one separately to prevent attaching the wrong canister to the wrong plastic actuator. In this way, the patient can be sure to always know the correct number of remaining doses. Never attach a canister of medication from any other inhaler to the Albuterol Sulfate HFA actuator and never attach the Albuterol Sulfate HFA canister to an actuator from any other inhaler. If the mouthpiece becomes blocked, washing the mouthpiece will remove the blockage. If it is necessary to use the inhaler before it is completely dry, shake off excess water, replace canister, spray twice into the air away from face, and take the prescribed dose. After such use, the mouthpiece should be rewashed and allowed to air dry thoroughly. [see FDA-Approved Patient Labeling (17.9)] .

Dose Counter: Albuterol Sulfate HFA has a dose counter attached to the actuator. When the patient receives the inhaler, a black dot will appear in the viewing window until it has been primed 3 times, at which point the number 200 will be displayed. The dose counter will count down each time a spray is released. When the dose counter reaches 20, the color of the numbers will change to red to remind the patient to contact their pharmacist for a refill of medication or consult their physician for a prescription refill. When the dose counter reaches 0, the background will change to solid red. Albuterol Sulfate HFA inhaler should be discarded when the dose counter displays 0 or after the expiration date on the product, whichever comes first.

3 DOSAGE FORMS & STRENGTHS

Albuterol Sulfate HFA is an inhalation aerosol. Albuterol Sulfate HFA is supplied as an 8.5 g/200 actuations pressurized aluminum canister with a red plastic actuator with a dose counter and white dust cap each in boxes of one. Each actuation delivers 120 mcg of albuterol sulfate from the canister valve and 108 mcg of albuterol sulfate from the actuator mouthpiece (equivalent to 90 mcg of albuterol base).

4 CONTRAINDICATIONS

Albuterol Sulfate HFA Inhalation Aerosol is contraindicated in patients with a history of hypersensitivity to albuterol and any other Albuterol Sulfate HFA Inhalation Aerosol components. Rare cases of hypersensitivity reactions, including urticaria, angioedema, and rash have been reported after the use of albuterol sulfate [see Warnings and Precautions (5.6)] .

5 WARNINGS & PRECAUTIONS

5.1 Paradoxical Bronchospasm

Albuterol Sulfate HFA Inhalation Aerosol can produce paradoxical bronchospasm that may be life threatening. If paradoxical bronchospasm occurs, Albuterol Sulfate HFA Inhalation Aerosol should be discontinued immediately and alternative therapy instituted. It should be recognized that paradoxical bronchospasm, when associated with inhaled formulations, frequently occurs with the first use of a new canister.

5.2 Deterioration of Asthma

Asthma may deteriorate acutely over a period of hours or chronically over several days or longer. If the patient needs more doses of Albuterol Sulfate HFA Inhalation Aerosol than usual, this may be a marker of destabilization of asthma and requires re-evaluation of the patient and treatment regimen, giving special consideration to the possible need for anti-inflammatory treatment, e.g., corticosteroids.

5.3 Use of Anti-inflammatory Agents

The use of beta-adrenergic-agonist bronchodilators alone may not be adequate to control asthma in many patients. Early consideration should be given to adding anti-inflammatory agents, e.g., corticosteroids, to the therapeutic regimen.

5.4 Cardiovascular Effects

Albuterol Sulfate HFA Inhalation Aerosol, like other beta-adrenergic agonists, can produce clinically significant cardiovascular effects in some patients as measured by pulse rate, blood pressure, and/or symptoms. Although such effects are uncommon after administration of Albuterol Sulfate HFA Inhalation Aerosol at recommended doses, if they occur, the drug may need to be discontinued. In addition, beta-agonists have been reported to produce ECG changes, such as flattening of the T wave, prolongation of the QTc interval, and ST segment depression. The clinical significance of these findings is unknown. Therefore, Albuterol Sulfate HFA Inhalation Aerosol, like all sympathomimetic amines, should be used with caution in patients with cardiovascular disorders, especially coronary insufficiency, cardiac arrhythmias, and hypertension.

5.5 Do Not Exceed Recommended Dose

Fatalities have been reported in association with excessive use of inhaled sympathomimetic drugs in patients with asthma. The exact cause of death is unknown, but cardiac arrest following an unexpected development of a severe acute asthmatic crisis and subsequent hypoxia is suspected.

5.6 Immediate Hypersensitivity Reactions

Immediate hypersensitivity reactions may occur after administration of albuterol sulfate, as demonstrated by rare cases of urticaria, angioedema, rash, bronchospasm, anaphylaxis, and oropharyngeal edema. The potential for hypersensitivity must be considered in the clinical evaluation of patients who experience immediate hypersensitivity reactions while receiving Albuterol Sulfate HFA Inhalation Aerosol.

5.7 Coexisting Conditions

Albuterol Sulfate HFA Inhalation Aerosol, like all sympathomimetic amines, should be used with caution in patients with cardiovascular disorders, especially coronary insufficiency, cardiac arrhythmias, and hypertension; in patients with convulsive disorders, hyperthyroidism, or diabetes mellitus; and in patients who are unusually responsive to sympathomimetic amines. Clinically significant changes in systolic and diastolic blood pressure have been seen in individual patients and could be expected to occur in some patients after use of any beta-adrenergic bronchodilator. Large doses of intravenous albuterol have been reported to aggravate preexisting diabetes mellitus and ketoacidosis.

5.8 Hypokalemia

As with other beta-agonists, Albuterol Sulfate HFA Inhalation Aerosol may produce significant hypokalemia in some patients, possibly through intracellular shunting, which has the potential to produce adverse cardiovascular effects. The decrease is usually transient, not requiring supplementation.

6 ADVERSE REACTIONS

Use of Albuterol Sulfate HFA may be associated with the following:

- Paradoxical bronchospasm [see Warnings and Precautions (5.1)]
- Cardiovascular Effects [see Warnings and Precautions (5.4)]
- Immediate hypersensitivity reactions [see Warnings and Precautions (5.6)]
- Hypokalemia [see Warnings and Precautions (5.8)]

6.1 Clinical Trials Experience

A total of 1090 subjects were treated with Albuterol Sulfate HFA Inhalation Aerosol, or with the same formulation of albuterol as in Albuterol Sulfate HFA Inhalation Aerosol, during the worldwide clinical development program.

Because clinical trials are conducted under widely varying conditions, adverse reaction rates observed in the clinical trials of a drug cannot be directly compared to rates in the clinical trials of another drug and may not reflect the rates observed in practice.

Adult and Adolescents 12 Years of Age and Older: The adverse reaction information presented in the table below concerning Albuterol Sulfate HFA Inhalation Aerosol is derived from a 6-week, blinded study which compared Albuterol Sulfate HFA Inhalation Aerosol (180 mcg four times daily) with a double-blinded matched placebo HFA-Inhalation Aerosol and an evaluator-blinded marketed active comparator HFA-134a albuterol inhaler in 172 asthmatic patients 12 to 76 years of age. The table lists the incidence of all adverse events (whether considered by the investigator drug related or unrelated to drug) from this study which occurred at a rate of 3% or greater in the Albuterol Sulfate HFA Inhalation Aerosol treatment group and more frequently in the Albuterol Sulfate HFA Inhalation Aerosol treatment group than in the matched placebo group. Overall, the incidence and nature of the adverse events reported for Albuterol Sulfate HFA Inhalation Aerosol and the marketed active comparator HFA-134a albuterol inhaler were comparable.

Adverse Experience Incidences (% of Patients) in a Six-Week Clinical Trial [This table includes all adverse events (whether considered by the investigator drug related or unrelated to drug) which occurred at an incidence rate of at least 3.0% in the Albuterol Sulfate HFA Inhalation Aerosol group and more frequently in the Albuterol Sulfate HFA Inhalation Aerosol group than in the placebo HFA Inhalation Aerosol group.]
Body System/ Adverse Event (as Preferred Term) |  | Albuterol Sulfate HFA Inhalation Aerosol (N = 58) | Marketed active comparator HFA-134a albuterol inhaler (N = 56) | Matched Placebo HFA-134a Inhalation Aerosol (N = 58)
Body as a Whole | Headache | 7 | 5 | 2
Cardiovascular | Tachycardia | 3 | 2 | 0
Musculoskeletal | Pain | 3 | 0 | 0
Nervous System | Dizziness | 3 | 0 | 0
Respiratory System | Pharyngitis | 14 | 7 | 9
Respiratory System | Rhinitis | 5 | 4 | 2

Adverse events reported by less than 3% of the patients receiving Albuterol Sulfate HFA Inhalation Aerosol but by a greater proportion of Albuterol Sulfate HFA Inhalation Aerosol patients than the matched placebo patients, which have the potential to be related to Albuterol Sulfate HFA Inhalation Aerosol, included chest pain, infection, diarrhea, glossitis, accidental injury (nervous system), anxiety, dyspnea, ear disorder, ear pain, and urinary tract infection.

In small cumulative dose studies, tremor, nervousness, and headache were the most frequently occurring adverse events.

Pediatric Patients 4 to 11 Years of Age: Adverse events reported in a 3-week pediatric clinical trial comparing the same formulation of albuterol as in Albuterol Sulfate HFA Inhalation Aerosol (180 mcg albuterol four times daily) to a matching placebo HFA inhalation aerosol occurred at a low incidence rate (no greater than 2% in the active treatment group) and were similar to those seen in adult and adolescent trials.

6.2 Postmarketing Experience

The following adverse reactions have been identified during postapproval use of Albuterol Sulfate HFA. Because these reactions are reported voluntarily from a population of uncertain size, it is not always possible to reliably estimate their frequency or establish a causal relationship to drug exposure. Reports have included rare cases of aggravated bronchospasm, lack of efficacy, asthma exacerbation (reported fatal in one case), muscle cramps, and various oropharyngeal side-effects such as throat irritation, altered taste, glossitis, tongue ulceration, and gagging.

The following adverse events have been observed in postapproval use of inhaled albuterol: urticaria, angioedema, rash, bronchospasm, hoarseness, oropharyngeal edema, and arrhythmias (including atrial fibrillation, supraventricular tachycardia, extrasystoles). In addition, albuterol, like other sympathomimetic agents, can cause adverse reactions such as: angina, hypertension or hypotension, palpitations, central nervous system stimulation, insomnia, headache, nervousness, tremor, muscle cramps, drying or irritation of the oropharynx, hypokalemia, hyperglycemia, and metabolic acidosis.

7 DRUG INTERACTIONS

Other short-acting sympathomimetic aerosol bronchodilators should not be used concomitantly with Albuterol Sulfate HFA Inhalation Aerosol. If additional adrenergic drugs are to be administered by any route, they should be used with caution to avoid deleterious cardiovascular effects.

7.1 Beta-Blockers

Beta-adrenergic-receptor blocking agents not only block the pulmonary effect of beta-agonists, such as Albuterol Sulfate HFA Inhalation Aerosol, but may produce severe bronchospasm in asthmatic patients. Therefore, patients with asthma should not normally be treated with beta-blockers. However, under certain circumstances, e.g., as prophylaxis after myocardial infarction, there may be no acceptable alternatives to the use of beta-adrenergic-blocking agents in patients with asthma. In this setting, consider cardioselective beta-blockers, although they should be administered with caution.

7.2 Diuretics

The ECG changes and/or hypokalemia which may result from the administration of non-potassium sparing diuretics (such as loop or thiazide diuretics) can be acutely worsened by beta-agonists, especially when the recommended dose of the beta-agonist is exceeded. Although the clinical significance of these effects is not known, caution is advised in the coadministration of beta-agonists with non-potassium sparing diuretics. Consider monitoring potassium levels.

7.3 Digoxin

Mean decreases of 16% and 22% in serum digoxin levels were demonstrated after single dose intravenous and oral administration of albuterol, respectively, to normal volunteers who had received digoxin for 10 days. The clinical significance of these findings for patients with obstructive airway disease who are receiving albuterol and digoxin on a chronic basis is unclear. Nevertheless, it would be prudent to carefully evaluate the serum digoxin levels in patients who are currently receiving digoxin and Albuterol Sulfate HFA Inhalation Aerosol.

7.4 Monoamine Oxidase Inhibitors or Tricyclic Antidepressants

Albuterol Sulfate HFA Inhalation Aerosol should be administered with extreme caution to patients being treated with monoamine oxidase inhibitors or tricyclic antidepressants, or within 2 weeks of discontinuation of such agents, because the action of albuterol on the cardiovascular system may be potentiated. Consider alternative therapy in patients taking MAO inhibitors or tricyclic antidepressants.

8 USE IN SPECIFIC POPULATIONS

8.1 Pregnancy

Pregnancy Exposure Registry

There is a pregnancy exposure registry that monitors pregnancy outcomes in women exposed to asthma medications during pregnancy. For more information, contact the Mothers To Baby Pregnancy Studies conducted by the Organization of Teratology Information Specialists at 1-877-311-8972 or visit http://mothertobaby.org/pregnancy-studies/.

Risk Summary

There are no randomized clinical studies of use of albuterol during pregnancy. Available data from published epidemiological studies and postmarketing case reports of pregnancy outcomes following inhaled albuterol use do not consistently demonstrate a risk of major birth defects or miscarriage. There are clinical considerations with use of albuterol in pregnant women [see Clinical Considerations]. In animal reproduction studies, when albuterol sulfate was administered subcutaneously to pregnant mice there was evidence of cleft palate at less than and up to 9 times the maximum recommended human daily inhalation dose (MRHDID) [see Data].

The estimated background risk of major birth defects and miscarriage for the indicated population(s) are unknown. In the U.S. general population, the estimated risk of major birth defects and miscarriage in clinically recognized pregnancies is 2 to 4% and 15 to 20%, respectively.

Clinical Considerations

Disease-Associated Maternal and/or Embryo/Fetal Risk

In women with poorly or moderately controlled asthma, there is an increased risk of preeclampsia in the mother and prematurity, low birth weight, and small for gestational age in the neonate. Pregnant women should be closely monitored and medication adjusted as necessary to maintain optimal control.

Labor or Delivery

Because of the potential for beta-agonist interference with uterine contractility, use of Albuterol Sulfate HFA Inhalation Aerosol for relief of bronchospasm during labor should be restricted to those patients in whom the benefits clearly outweigh the risk. Albuterol Sulfate HFA Inhalation Aerosol has not been approved for the management of pre-term labor. Serious adverse reactions, including pulmonary edema, have been reported during or following treatment of premature labor with beta2-agonists, including albuterol.

Data

Animal Data

In a mouse reproduction study, subcutaneously administered albuterol sulfate produced cleft palate formation in 5 of 111 (4.5%) fetuses at an exposure nine-tenths of the MRHDID for adults (on a mg/m^2 basis at a maternal dose of 0.25 mg/kg) and in 10 of 108 (9.3%) fetuses at approximately 9 times the MRHDID (on a mg/m^2 basis at a maternal dose of 2.5 mg/kg). Similar effects were not observed at approximately one-eleventh the MRHDID for adults (on a mg/m^2 basis at a maternal dose of 0.025 mg/kg). Cleft palate also occurred in 22 of 72 (30.5%) fetuses from females treated subcutaneously with isoproterenol (positive control).

In a rabbit reproduction study, orally administered albuterol sulfate induced cranioschisis in 7 of 19 fetuses (37%) at approximately 750 times the MRHDID (on a mg/m^2 basis at a maternal dose of 50 mg/kg).

In a rat reproduction study, an albuterol sulfate/HFA-134a formulation administered by inhalation did not produce any teratogenic effects at exposures approximately 80 times the MRHDID (on a mg/m^2 basis at a maternal dose of 10.5 mg/kg).

A study in which pregnant rats were dosed with radiolabeled albuterol sulfate demonstrated that drug-related material is transferred from the maternal circulation to the fetus.

8.2 Lactation

Risk Summary

There are no available data on the presence of albuterol in human milk, the effects on the breastfed child, or the effects on milk production. However, plasma levels of albuterol after inhaled therapeutic doses are low in humans, and if present in breast milk, albuterol has a low oral bioavailability [see Clinical Pharmacology (12.3)].

The developmental and health benefits of breastfeeding should be considered along with the mother’s clinical need for albuterol and any potential adverse effects on the breastfed child from albuterol or from the underlying maternal condition.

8.4 Pediatric Use

The safety and effectiveness of Albuterol Sulfate HFA Inhalation Aerosol for the treatment or prevention of bronchospasm in children 12 years of age and older with reversible obstructive airway disease is based on one 6-week clinical trial in 116 patients 12 years of age and older with asthma comparing doses of 180 mcg four times daily with placebo, and one single-dose crossover study comparing doses of 90, 180, and 270 mcg with placebo in 58 patients [see Clinical Studies (14.1)] . The safety and effectiveness of Albuterol Sulfate HFA Inhalation Aerosol for treatment of exercise-induced bronchospasm in children 12 years of age and older is based on one single-dose crossover study in 24 adults and adolescents with exercise-induced bronchospasm comparing doses of 180 mcg with placebo [see Clinical Studies (14.2)].

The safety of Albuterol Sulfate HFA Inhalation Aerosol in children 4 to 11 years of age is based on one 3-week clinical trial in 50 patients 4 to 11 years of age with asthma using the same formulation of albuterol as in Albuterol Sulfate HFA Inhalation Aerosol comparing doses of 180 mcg four times daily with placebo. The effectiveness of Albuterol Sulfate HFA Inhalation Aerosol in children 4 to 11 years of age is extrapolated from clinical trials in patients 12 years of age and older with asthma and exercise-induced bronchospasm, based on data from a single-dose study comparing the bronchodilatory effect of Albuterol Sulfate HFA 90 mcg and 180 mcg with placebo in 55 patients with asthma and a 3-week clinical trial using the same formulation of albuterol as in Albuterol Sulfate HFA Inhalation Aerosol in 95 asthmatic children 4 to 11 years of age comparing a dose of 180 mcg albuterol four times daily with placebo [see Clinical Studies (14.1)].

The safety and effectiveness of Albuterol Sulfate HFA Inhalation Aerosol in pediatric patients below the age of 4 years have not been established.

8.5 Geriatric Use

Clinical studies of Albuterol Sulfate HFA Inhalation Aerosol did not include sufficient numbers of patients aged 65 and over to determine whether they respond differently from younger patients. Other reported clinical experience has not identified differences in responses between elderly and younger patients. In general, dose selection for an elderly patient should be cautious, usually starting at the low end of the dosing range, reflecting the greater frequency of decreased hepatic, renal, or cardiac function, and of concomitant disease or other drug therapy [see Warnings and Precautions (5.4, 5.7)] .

All beta2-adrenergic agonists, including albuterol, are known to be substantially excreted by the kidney, and the risk of toxic reactions may be greater in patients with impaired renal function. Because elderly patients are more likely to have decreased renal function, care should be taken in dose selection, and it may be useful to monitor renal function.

10 OVERDOSAGE

The expected symptoms with overdosage are those of excessive beta-adrenergic stimulation and/or occurrence or exaggeration of any of the symptoms listed under ADVERSE REACTIONS, e.g., seizures, angina, hypertension or hypotension, tachycardia with rates up to 200 beats per minute, arrhythmias, nervousness, headache, tremor, dry mouth, palpitation, nausea, dizziness, fatigue, malaise, and insomnia.

Hypokalemia may also occur. As with all sympathomimetic medications, cardiac arrest and even death may be associated with abuse of Albuterol Sulfate HFA Inhalation Aerosol.

Treatment consists of discontinuation of Albuterol Sulfate HFA Inhalation Aerosol together with appropriate symptomatic therapy. The judicious use of a cardioselective beta-receptor blocker may be considered, bearing in mind that such medication can produce bronchospasm. There is insufficient evidence to determine if dialysis is beneficial for overdosage of Albuterol Sulfate HFA Inhalation Aerosol.

The oral median lethal dose of albuterol sulfate in mice is greater than 2,000 mg/kg (approximately 6,800 times the maximum recommended daily inhalation dose for adults on a mg/m^2 basis and approximately 3,200 times the maximum recommended daily inhalation dose for children on a mg/m^2 basis). In mature rats, the subcutaneous median lethal dose of albuterol sulfate is approximately 450 mg/kg (approximately 3,000 times the maximum recommended daily inhalation dose for adults on a mg/m^2 basis and approximately 1,400 times the maximum recommended daily inhalation dose for children on a mg/m^2 basis). In young rats, the subcutaneous median lethal dose is approximately 2,000 mg/kg (approximately 14,000 times the maximum recommended daily inhalation dose for adults on a mg/m^2 basis and approximately 6,400 times the maximum recommended daily inhalation dose for children on a mg/m^2 basis). The inhalation median lethal dose has not been determined in animals.

11 DESCRIPTION

The active ingredient of Albuterol Sulfate HFA Inhalation Aerosol is albuterol sulfate, a racemic salt, of albuterol. Albuterol sulfate has the chemical name α^1-[(tert-butylamino) methyl]-4-hydroxy- m-xylene-α,α'-diol sulfate (2:1) (salt), and has the following chemical structure:

The molecular weight of albuterol sulfate is 576.7, and the empirical formula is (C13H21NO3)2•H2SO4. Albuterol sulfate is a white to off-white crystalline powder. It is soluble in water and slightly soluble in ethanol. Albuterol sulfate is the official generic name in the United States, and salbutamol sulfate is the World Health Organization recommended generic name. Albuterol Sulfate HFA Inhalation Aerosol is a pressurized metered-dose aerosol unit with a dose counter. Albuterol Sulfate HFA is for oral inhalation only. It contains a microcrystalline suspension of albuterol sulfate in propellant HFA-134a (1, 1, 1, 2-tetrafluoroethane) and ethanol.

Prime the inhaler before using for the first time and in cases where the inhaler has not been used for more than 2 weeks by releasing three sprays into the air, away from the face. After priming, each actuation delivers 108 mcg albuterol sulfate, from the actuator mouthpiece (equivalent to 90 mcg of albuterol base). Each canister provides 200 actuations (inhalations).

This product does not contain chlorofluorocarbons (CFCs) as the propellant.

12 CLINICAL PHARMACOLOGY

12.1 Mechanism of Action

Albuterol sulfate is a beta2-adrenergic agonist. The pharmacologic effects of albuterol sulfate are attributable to activation of beta2-adrenergic receptors on airway smooth muscle. Activation of beta2-adrenergic receptors leads to the activation of adenylcyclase and to an increase in the intracellular concentration of cyclic-3', 5'-adenosine monophosphate (cyclic AMP). This increase of cyclic AMP is associated with the activation of protein kinase A, which in turn inhibits the phosphorylation of myosin and lowers intracellular ionic calcium concentrations, resulting in muscle relaxation. Albuterol relaxes the smooth muscle of all airways, from the trachea to the terminal bronchioles. Albuterol acts as a functional antagonist to relax the airway irrespective of the spasmogen involved, thus protecting against all bronchoconstrictor challenges. Increased cyclic AMP concentrations are also associated with the inhibition of release of mediators from mast cells in the airway. While it is recognized that beta2-adrenergic receptors are the predominant receptors on bronchial smooth muscle, data indicate that there are beta-receptors in the human heart, 10% to 50% of which are cardiac beta2-adrenergic receptors. The precise function of these receptors has not been established [see Warnings and Precautions (5.4)] .

Albuterol has been shown in most controlled clinical trials to have more effect on the respiratory tract, in the form of bronchial smooth muscle relaxation, than isoproterenol at comparable doses while producing fewer cardiovascular effects. However, inhaled albuterol, like other beta-adrenergic agonist drugs, can produce a significant cardiovascular effect in some patients, as measured by pulse rate, blood pressure, symptoms, and/or electrocardiographic changes [see Warnings and Precautions (5.4)] .

12.2 Pharmacokinetics

The systemic levels of albuterol are low after inhalation of recommended doses. In a crossover study conducted in healthy male and female volunteers, high cumulative doses of Albuterol Sulfate HFA Inhalation Aerosol (1,080 mcg of albuterol base administered over one hour) yielded mean peak plasma concentrations (Cmax) and systemic exposure (AUCinf) of approximately 4,100 pg/mL and 28,426 pg/mL*hr, respectively compared to approximately 3,900 pg/mL and 28,395 pg/mL*hr, respectively following the same dose of an active HFA-134a albuterol inhaler comparator. The terminal plasma half-life of albuterol delivered by Albuterol Sulfate HFA Inhalation Aerosol was approximately 6 hours. Comparison of the pharmacokinetic parameters demonstrated no differences between the products.

The pharmacokinetic profile of Albuterol Sulfate HFA Inhalation Aerosol was evaluated in a two-way cross-over study in 11 healthy pediatric volunteers, 4 to 11 years of age. A single dose administration of Albuterol Sulfate HFA Inhalation Aerosol (180 mcg albuterol base) yielded a least square mean (SE) Cmax and AUC0-∞ of 1,100 (1.18) pg/mL and 5,120 (1.15) pg/mL*hr, respectively. The least square mean (SE) terminal plasma half-life of albuterol delivered by Albuterol Sulfate HFA Inhalation Aerosol was 166 (7.8) minutes.

Metabolism and Elimination: Information available in the published literature suggests that the primary enzyme responsible for the metabolism of albuterol in humans is SULTIA3 (sulfotransferase). When racemic albuterol was administered either intravenously or via inhalation after oral charcoal administration, there was a 3- to 4-fold difference in the area under the concentration-time curves between the (R)- and (S)-albuterol enantiomers, with (S)-albuterol concentrations being consistently higher. However, without charcoal pretreatment, after either oral or inhalation administration the differences were 8- to 24-fold, suggesting that the (R)-albuterol is preferentially metabolized in the gastrointestinal tract, presumably by SULTIA3.

The primary route of elimination of albuterol is through renal excretion (80% to 100%) of either the parent compound or the primary metabolite. Less than 20% of the drug is detected in the feces. Following intravenous administration of racemic albuterol, between 25% and 46% of the (R)-albuterol fraction of the dose was excreted as unchanged (R)-albuterol in the urine.

Geriatric, Pediatric, Hepatic/Renal Impairment: No pharmacokinetic studies for Albuterol Sulfate HFA Inhalation Aerosol have been conducted in neonates or elderly subjects.

The effect of hepatic impairment on the pharmacokinetics of Albuterol Sulfate HFA Inhalation Aerosol has not been evaluated.

The effect of renal impairment on the pharmacokinetics of albuterol was evaluated in 5 subjects with creatinine clearance of 7 to 53 mL/min, and the results were compared with those from healthy volunteers. Renal disease had no effect on the half-life, but there was a 67% decline in albuterol clearance. Caution should be used when administering high doses of Albuterol Sulfate HFA Inhalation Aerosol to patients with renal impairment [see Use in Specific Populations (8.5)] .

13 NONCLINICAL TOXICOLOGY

13.1 Carcinogenesis, Mutagenesis, Impairment of Fertility

In a 2‑year study in Sprague-Dawley rats, albuterol sulfate caused a dose-related increase in the incidence of benign leiomyomas of the mesovarium at and above dietary doses of 2 mg/kg (approximately 15 times and 6 times the maximum recommended human daily inhalation dose (MRHDID) for adults and children, respectively, on a mg/m^2 basis). In another study this effect was blocked by the coadministration of propranolol, a non-selective beta-adrenergic antagonist. In an 18‑month study in CD‑1 mice, albuterol sulfate showed no evidence of tumorigenicity at dietary doses of up to 500 mg/kg (approximately 1,900 times and 740 times the MRHDID for adults and children, respectively, on a mg/m^2 basis). In a 22‑month study in Golden Hamsters, albuterol sulfate showed no evidence of tumorigenicity at dietary doses of up to 50 mg/kg (approximately 250 times and 100 times the MRHDID for adults and children, respectively, on a mg/m^2 basis).

Albuterol sulfate was not mutagenic in the Ames test or a mutation test in yeast. Albuterol sulfate was not clastogenic in a human peripheral lymphocyte assay or in an AH1 strain mouse micronucleus assay.

Reproduction studies in rats demonstrated no evidence of impaired fertility at oral doses up to 50 mg/kg (approximately 380 times the MRHDID for adults on a mg/m^2 basis).

13.2 Animal Toxicology and/or Pharmacology

Preclinical: Intravenous studies in rats with albuterol sulfate have demonstrated that albuterol crosses the blood-brain barrier and reaches brain concentrations amounting to approximately 5% of the plasma concentrations. In structures outside the blood-brain barrier (pineal and pituitary glands), albuterol concentrations were found to be 100 times those in the whole brain.

Studies in laboratory animals (minipigs, rodents, and dogs) have demonstrated the occurrence of cardiac arrhythmias and sudden death (with histologic evidence of myocardial necrosis) when b‑agonists and methylxanthines were administered concurrently. The clinical significance of these findings is unknown.

Propellant HFA‑134a is devoid of pharmacological activity except at very high doses in animals (380 ‑ 1300 times the maximum human exposure based on comparisons of AUC values), primarily producing ataxia, tremors, dyspnea, or salivation. These are similar to effects produced by the structurally related chlorofluorocarbons (CFCs), which have been used extensively in metered-dose inhalers.

In animals and humans, propellant HFA‑134a was found to be rapidly absorbed and rapidly eliminated, with an elimination half-life of 3 ‑ 27 minutes in animals and 5 ‑ 7 minutes in humans. Time to maximum plasma concentration (Tmax) and mean residence time are both extremely short leading to a transient appearance of HFA‑134a in the blood with no evidence of accumulation.

14 CLINICAL STUDIES

14.1 Bronchospasm Associated with Asthma

Adult and Adolescent Patients 12 Years of Age and Older: In a 6-week, randomized, double-blind, placebo-controlled trial, Albuterol Sulfate HFA Inhalation Aerosol (58 patients) was compared to a matched placebo HFA inhalation aerosol (58 patients) in asthmatic patients 12 to 76 years of age at a dose of 180 mcg albuterol four times daily. An evaluator-blind marketed active comparator HFA-134a albuterol inhaler arm (56 patients) was included.

Serial FEV1 measurements, shown below as percent change from test-day baseline at Day 1 and at Day 43, demonstrated that two inhalations of Albuterol Sulfate HFA Inhalation Aerosol produced significantly greater improvement in FEV1 over the pre-treatment value than the matched placebo, as well as a comparable bronchodilator effect to the marketed active comparator HFA-134a albuterol inhaler.

BOXED WARNING

FEV1 as Mean Percent Change from Test-Day Pre-Dose in a
6-Week Clinical Trial
Day 1

BOXED WARNING

Day 43

In this study, 31 of 58 patients treated with Albuterol Sulfate HFA Inhalation Aerosol achieved a 15% increase in FEV1 within 30 minutes post-dose on Day 1. In these patients, the median time to onset, median time to peak effect, and median duration of effect were 8.2 minutes, 47 minutes, and approximately 3 hours, respectively. In some patients, the duration of effect was as long as 6 hours.

In a placebo-controlled, single-dose, crossover study, Albuterol Sulfate HFA Inhalation Aerosol, administered at albuterol doses of 90, 180 and 270 mcg, produced bronchodilator responses significantly greater than those observed with a matched placebo HFA inhalation aerosol and comparable to a marketed active comparator HFA-134a albuterol inhaler.

Pediatric Patients 4 to 11 Years of Age: In a 3-week, randomized, double-blind, placebo-controlled trial, the same formulation of albuterol as in Albuterol Sulfate HFA Inhalation Aerosol (50 patients) was compared to a matched placebo HFA inhalation aerosol (45 patients) in asthmatic children 4 to 11 years of age at a dose of 180 mcg albuterol four times daily. Serial FEV1 measurements, expressed as the maximum percent change from test-day baseline in percent predicted FEV1 at Day 1 and at Day 22 observed within two hours post-dose, demonstrated that two inhalations of HFA albuterol sulfate produced significantly greater improvement in FEV1 over the pre-treatment value than the matched placebo.

In this study, 21 of 50 pediatric patients treated with the same formulation of albuterol as in Albuterol Sulfate HFA Inhalation Aerosol achieved a 15% increase in FEV1 within 30 minutes post-dose on Day 1. In these patients, the median time to onset, median time to peak effect and median duration of effect were 10 minutes, 31 minutes, and approximately 4 hours, respectively. In some pediatric patients, the duration of effect was as long as 6 hours.

In a placebo-controlled, single-dose, crossover study in 55 pediatric patients 4 to 11 years of age, Albuterol Sulfate HFA Inhalation Aerosol, administered at albuterol doses of 90 and 180 mcg, was compared with a matched placebo HFA inhalation aerosol. Serial FEV1 measurements, expressed as the baseline-adjusted percent predicted FEV1 observed over 6 hours post-dose, demonstrated that one and two inhalations of Albuterol Sulfate HFA Inhalation Aerosol produced significantly greater bronchodilator responses than the matched placebo.

14.2 Exercise-Induced Bronchospasm

In a randomized, single-dose, crossover study in 24 adults and adolescents with exercise-induced bronchospasm (EIB), two inhalations of Albuterol Sulfate HFA taken 30 minutes before exercise prevented EIB for the hour following exercise (defined as maintenance of FEV1 within 80% of post-dose, pre-exercise baseline values) in 83% (20 of 24) of patients as compared to 25% (6 of 24) of patients when they received placebo.

Some patients who participated in these clinical trials were using concomitant steroid therapy.

16 HOW SUPPLIED/STORAGE & HANDLING

Albuterol Sulfate HFA Inhalation Aerosol is supplied as a pressurized aluminum canister with a red plastic actuator with a dose counter and white dust cap each in boxes of one. Each canister contains 8.5 g of the formulation and provides 200 actuations (NDC 68071-4940-2).

SHAKE WELL BEFORE USE. Store between 15° and 25°C (59° and 77°F). Contents under pressure. Do not puncture or incinerate. Protect from freezing temperatures and prolonged exposure to direct sunlight. Exposure to temperatures above 120°F may cause bursting. For best results, canister should be at room temperature before use. Avoid spraying in eyes. Keep out of reach of children.

See FDA-Approved Patient Labeling (17.9) for priming and cleaning instructions.

The red actuator supplied with Albuterol Sulfate HFA Inhalation Aerosol should not be used with the canister from any other inhalation aerosol products. The Albuterol Sulfate HFA Inhalation Aerosol canister should not be used with the actuator from any other inhalation aerosol products.

Albuterol Sulfate HFA inhaler has a dose counter attached to the actuator. Patients should never try to alter the numbers for the dose counter or tamper with the pin mechanism inside the actuator. Discard the Albuterol Sulfate HFA inhaler when the counter displays 0 or after the expiration date on the product, whichever comes first. The labeled amount of medication in each actuation cannot be assured after the counter displays 0, even though the canister is not completely empty and will continue to operate. Never immerse the canister into water to determine how full the canister is ("float test").

Albuterol Sulfate HFA Inhalation Aerosol does not contain chlorofluorocarbons (CFCs) as the propellant.

17 PATIENT COUNSELING INFORMATION

See FDA-Approved Patient Labeling (17.9)

Patients should be given the following information:

17.1 Frequency of Use

The action of Albuterol Sulfate HFA Inhalation Aerosol should last for 4 to 6 hours. Do not use Albuterol Sulfate HFA Inhalation Aerosol more frequently than recommended. Instruct patients to not increase the dose or frequency of doses of Albuterol Sulfate HFA Inhalation Aerosol without consulting the physician. If patients find that treatment with Albuterol Sulfate HFA Inhalation Aerosol becomes less effective for symptomatic relief, symptoms become worse, and/or they need to use the product more frequently than usual, they should seek medical attention immediately.

17.2 Priming and Cleaning

Priming: Priming is essential to ensure appropriate albuterol content in each actuation. Instruct patients to prime the inhaler before using for the first time and in cases where the inhaler has not been used for more than 2 weeks by releasing three sprays into the air, away from the face.

Cleaning: To ensure proper dosing and prevent actuator orifice blockage, instruct patients to wash the red plastic actuator mouthpiece and dry thoroughly at least once a week. Instruct patients that if they have more than one Albuterol Sulfate HFA inhaler, they should wash each one at separate times to prevent attaching the wrong canister to the wrong plastic actuator. In this way, they can be sure they will always know the correct number of remaining doses. Patients should be instructed to never attach a canister of medicine from any other inhaler to the Albuterol Sulfate HFA actuator and never attach the Albuterol Sulfate HFA canister to an actuator from any other inhaler. Patients should not remove the canister from the actuator except during cleaning because reattachment may release a dose into the air and the dose counter will count down each time a spray is released. Detailed cleaning instructions are included in the illustrated Information for the Patient leaflet.

17.3 Dose Counter

Patients should be informed that Albuterol Sulfate HFA has a dose counter attached to the actuator. When the patient receives the inhaler, a black dot will appear in the viewing window until it has been primed 3 times, at which point the number 200 will be displayed. The dose counter will count down each time a spray is released. The dose-counter window displays the number of sprays left in the inhaler in units of two (e.g., 200, 198, 196, etc). When the counter displays 20, the color of the numbers will change to red to remind the patient to contact their pharmacist for a refill of medication or consult their physician for a prescription refill. When the dose counter reaches 0, the background will change to solid red. Patients should be informed to discard Albuterol Sulfate HFA inhaler when the dose counter displays 0 or after the expiration date on the product, whichever comes first.

17.4 Paradoxical Bronchospasm

Inform patients that Albuterol Sulfate HFA Inhalation Aerosol can produce paradoxical bronchospasm. Instruct patients to discontinue Albuterol Sulfate HFA Inhalation Aerosol if paradoxical bronchospasm occurs.

17.5 Concomitant Drug Use

While patients are taking Albuterol Sulfate HFA Inhalation Aerosol, other inhaled drugs and asthma medications should be taken only as directed by a physician.

17.6 Common Adverse Events

Common adverse effects of treatment with inhaled albuterol include palpitations, chest pain, rapid heart rate, tremor, or nervousness.

17.7 Pregnancy

Patients who are pregnant or nursing should contact their physician about the use of Albuterol Sulfate HFA Inhalation Aerosol.

There is a pregnancy exposure registry that monitors pregnancy outcomes in women exposed to asthma medications during pregnancy [see Use in Specific Populations (8.1)] .

17.8 General Information on Use

Effective and safe use of Albuterol Sulfate HFA Inhalation Aerosol includes an understanding of the way that it should be administered.

Shake well before each spray.

Use Albuterol Sulfate HFA Inhalation Aerosol only with the actuator supplied with the product. Discard the Albuterol Sulfate HFA inhaler when the dose counter displays 0 or after the expiration date on the product, whichever comes first. Never immerse the canister in water to determine how full the canister is ("float test").

In general, the technique for administering Albuterol Sulfate HFA Inhalation Aerosol to children is similar to that for adults. Children should use Albuterol Sulfate HFA Inhalation Aerosol under adult supervision, as instructed by the patient's physician .

17.9 FDA-Approved Patient Labeling

See tear-off illustrated Information for the Patient leaflet.

Mktd by: Teva Pharmaceuticals USA, Inc.

North Wales, PA 19454

Mfd by: IVAX Pharmaceuticals Ireland

Waterford, Ireland

Copyright ©2019, Teva Pharmaceuticals USA, Inc.

All rights reserved.

03/2019

ASHFA-003

Patient Information

Albuterol Sulfate HFA
Inhalation Aerosol

Read this Patient Information before you start using Albuterol Sulfate HFA and each time you get a refill. There may be new information. This information does not take the place of talking to your doctor about your medical condition or your treatment.

What is Albuterol Sulfate HFA?

Albuterol Sulfate HFA is a prescription medicine used in people 4 years of age and older to:

- treat or prevent bronchospasm in people who have reversible obstructive airway disease
- prevent exercise induced bronchospasm

It is not known if Albuterol Sulfate HFA is safe and effective in children under 4 years of age.

Who should not use Albuterol Sulfate HFA?

Do not use Albuterol Sulfate HFA if you are allergic to albuterol sulfate or any of the ingredients in Albuterol Sulfate HFA. See the end of this leaflet for a complete list of ingredients in Albuterol Sulfate HFA.

What should I tell my doctor before I use Albuterol Sulfate HFA?

Before you use Albuterol Sulfate HFA, tell your doctor if you:

- have heart problems
- have high blood pressure (hypertension)
- have convulsions (seizures)
- have thyroid problems
- have diabetes
- have low potassium levels in your blood
- are pregnant or plan to become pregnant. It is not known if Albuterol Sulfate HFA will harm your unborn baby. Talk to your doctor if you are pregnant or plan to become pregnant.
- are breastfeeding or plan to breastfeed. It is not known if Albuterol Sulfate HFA passes into your breast milk. Talk to your doctor about the best way to feed your baby if you are using Albuterol Sulfate HFA.

Tell your doctor about all the medicines you take, including prescription and non-prescription medicines, vitamins, and herbal supplements.

Albuterol Sulfate HFA and other medicines may affect each other and cause side effects. Albuterol Sulfate HFA may affect the way other medicines work, and other medicines may affect the way Albuterol Sulfate HFA works.

Especially tell your doctor if you take:

- other inhaled medicines or asthma medicines
- beta blocker medicines
- diuretics
- digoxin
- monoamine oxidase inhibitors
- tricyclic antidepressants

Ask your doctor or pharmacist for a list of these medicines if you are not sure.

Know the medicines you take. Keep a list of them to show your doctor and pharmacist when you get a new medicine.

How should I use Albuterol Sulfate HFA?

- For detailed instructions, see " Instructions for Use" at the end of this Patient Information.
- Use Albuterol Sulfate HFA exactly as your doctor tells you to use it.
- If your child needs to use Albuterol Sulfate HFA, watch your child closely to make sure your child uses the inhaler correctly. Your doctor will show you how your child should use Albuterol Sulfate HFA.
- Each dose of Albuterol Sulfate HFA should last up to 4 hours to 6 hours.
- Do not increase your dose or take extra doses of Albuterol Sulfate HFA without first talking to your doctor.
- Get medical help right away if Albuterol Sulfate HFA no longer helps your symptoms.
- Get medical help right away if your symptoms get worse or if you need to use your inhaler more often.
- While you are using Albuterol Sulfate HFA, do not use other inhaled rescue medicines and asthma medicines unless your doctor tells you to do so.
- Call your doctor if your asthma symptoms like wheezing and trouble breathing become worse over a few hours or days. Your doctor may need to give you another medicine (for example, corticosteroids) to treat your symptoms.

What are the possible side effects of Albuterol Sulfate HFA?

Albuterol Sulfate HFA may cause serious side effects, including:

- worsening trouble breathing, coughing and wheezing (paradoxical bronchospasm). If this happens stop using Albuterol Sulfate HFA and call your doctor or get emergency help right away. Paradoxical bronchospasm is more likely to happen with your first use of a new canister of medicine.
- heart problems including faster heart rate and higher blood pressure
- possible death in people with asthma who use too much Albuterol Sulfate HFA
- allergic reactions. Call your doctor right away if you have the following symptoms of an allergic reaction:
  - itchy skin
  - swelling beneath your skin or in your throat
  - rash
  - worsening trouble breathing
- low potassium levels in your blood
- worsening of other medical problems in people who also use Albuterol Sulfate HFA including increases in blood sugar

The most common side effects of Albuterol Sulfate HFA include:

- your heart feels like it is pounding or racing (palpitations)
- chest pain
- fast heart rate
- shakiness
- nervousness
- headache
- dizziness
- sore throat
- runny nose

Tell your doctor if you have any side effect that bothers you or that does not go away.

These are not all of the possible side effects of Albuterol Sulfate HFA. For more information, ask your doctor or pharmacist.

Call your doctor for medical advice about side effects. You may report side effects to FDA at 1-800-FDA-1088.

How should I store Albuterol Sulfate HFA?

- Store Albuterol Sulfate HFA at room temperature between 59° F and 77° F (15° C and 25° C).
- Avoid exposure to extreme heat and cold.
- Shake the Albuterol Sulfate HFA canister well before use.
- Do not puncture the Albuterol Sulfate HFA canister.
- Do not store the Albuterol Sulfate HFA canister near heat or a flame. Temperatures above 120° F may cause the canister to burst.
- Do not throw the Albuterol Sulfate HFA canister into a fire or an incinerator.
- Avoid spraying Albuterol Sulfate HFA in your eyes.

Keep Albuterol Sulfate HFA and all medicines out of the reach of children.

General Information about the safe and effective use of Albuterol Sulfate HFA

Medicines are sometimes prescribed for purposes other than those listed in a Medication Guide. Do not use Albuterol Sulfate HFA for a condition for which it was not prescribed. Do not give Albuterol Sulfate HFA to other people, even if they have the same symptoms that you have. It may harm them.

This Patient Information summarizes the most important information about Albuterol Sulfate HFA. If you would like more information, talk with your doctor. You can ask your pharmacist or doctor for information about Albuterol Sulfate HFA that is written for health professionals .

For more information, call 1-888-482-9522.

What are the ingredients in Albuterol Sulfate HFA?

Active ingredient: albuterol sulfate

Inactive ingredients: propellant HFA-134a and ethanol.

ASHFAPL-002

Rev. 1/2018

Instructions for Use

Albuterol Sulfate HFA
Inhalation Aerosol

Read this Instructions for Use before you start using Albuterol Sulfate HFA and each time you get a refill. There may be new information. This information does not take the place of talking to your doctor about your medical condition or your treatment.

The Parts of Your Albuterol Sulfate HFA Inhaler Device:

There are 2 main parts of your Albuterol Sulfate HFA inhaler device including a:

- red plastic actuator that sprays the medicine from the canister. See Figure A.
- protective dust cap that covers the mouthpiece of the actuator. See Figure A.

There is also a metal canister that holds the medicine. See Figure A.

There is also a dose counter attached to the back of the actuator with a viewing window that shows you how many sprays of medicine you have left. See Figure B.

You will see a black dot in the viewing window on the actuator until the device has been primed 3 times. See Figure B and " Priming Your Albuterol Sulfate HFA Device" below.

Figure A

Figure B

- Do not use the Albuterol Sulfate HFA actuator with a canister of medicine from any other inhaler.
- Do not use an Albuterol Sulfate HFA canister with an actuator from any other inhaler, including another Albuterol Sulfate HFA inhaler.

Priming Your Albuterol Sulfate HFA Device:

Your Albuterol Sulfate HFA device must be primed before you use it for the first time or if your device has not been used for more than 14 days in a row. Do not prime your Albuterol Sulfate HFA device every day.

- Remove your Albuterol Sulfate HFA device from its package.
- Remove the protective dust cap from the mouthpiece.
- Shake the inhaler well, and spray it into the air away from your face. See Figure C.

Figure C

- Shake and spray the inhaler like this 2 more times to finish priming it.
  The dose counter on the actuator should display the number 200 after you prime the actuator for the first time. See Figure D.

Figure D

Each Time You Use Your Albuterol Sulfate HFA Device:

- Make sure the canister fits firmly in the plastic actuator.
- Look into the mouthpiece to make sure there are no foreign objects there, especially if the cap has not been used to cover the mouthpiece.

Reading the Dose Counter on Your Albuterol Sulfate HFA Actuator

- The dose counter will count down each time a spray is released. The dose counter window shows the number of sprays left in your inhaler in units of 2 sprays. For example, there are 190 sprays left if the arrow is exactly opposite the number 190, or 189 sprays left if the arrow points between 190 and 188. See Figure D.
- When the dose counter reaches 0, it will continue to show 0 and you should replace your Albuterol Sulfate HFA device.
- The dose counter cannot be reset and is permanently attached to the actuator. Never change the numbers for the dose counter or touch the pin inside the actuator.
- Do not remove the canister from the plastic actuator except during cleaning. Reattaching the canister to the actuator may accidently release a dose of Albuterol Sulfate HFA into the air. The dose counter will count down each time a spray is released.

Using Your Albuterol Sulfate HFA Device:

Step 1. Shake the inhaler well before each spray. Take the cap off the mouthpiece of the actuator.

Step 2. Hold the inhaler with the mouthpiece down. See Figure E.

Figure E

Step 3. Breathe out through your mouth and push as much air from your lungs as you can. Put the mouthpiece in your mouth and close your lips around it. See Figure F.

Step 4. Push the top of the canister all the way down while you breathe in deeply and slowly through your mouth. See Figure F.

Figure F

Step 5. Right after the spray comes out, take your finger off the canister. After you have breathed in all the way, take the inhaler out of your mouth and close your mouth.

Step 6. Hold your breath as long as you can, up to 10 seconds, then breathe normally.
If your doctor has told you to use more sprays, wait 1 minute and shake the inhaler again. Repeat Steps 2 through Step 6.

Step 7. Put the cap back on the mouthpiece after every time you use the inhaler. Make sure the cap snaps firmly into place.

Cleaning Your Albuterol Sulfate HFA Device:

It is very important to keep the plastic actuator clean so the medicine will not build-up and block the spray. See Figure G and Figure H.

Figure G

Figure H

- Do not try to clean the metal canister or let it get wet. The inhaler may stop spraying if it is not cleaned correctly.
- If you have more than 1 Albuterol Sulfate HFA inhaler, wash each device at separate times to prevent putting the wrong canister together with the wrong plastic actuator. This way you can be sure you will always know the correct number of remaining doses of Albuterol Sulfate HFA.
- Wash the actuator at least 1 time each week as follows :
  - Take the canister out of the actuator, and take the cap off the mouthpiece.
  - Hold the actuator under the faucet and run warm water through it for about 30 seconds. See Figure I.
  - Figure I
  - Turn the actuator upside down and run warm water through the mouthpiece for about 30 seconds. See Figure J.
  - Figure J
  - Shake off as much water from the actuator as you can. Look into the mouthpiece to make sure any medicine build-up has been completely washed away. If there is any build-up, repeat the washing instructions.
  - Let the actuator air-dry completely, such as overnight. See Figure K.
  - Figure K
  - When the actuator is dry, put the canister in the actuator and make sure it fits firmly. Shake the inhaler well and spray it twice into the air away from your face. Put the cap back on the mouthpiece.

If you need to use your inhaler before the actuator is completely dry:

- Shake as much water off the actuator as you can.
- Put the canister in the actuator and make sure it fits firmly.
- Shake the inhaler well and spray it twice into the air away from your face.
- Take your Albuterol Sulfate HFA dose as prescribed.
- Follow the Cleaning Instructions above.

Replacing Your Albuterol Sulfate HFA Device

- When the dose counter on the actuator says the number 20, the color of the numbers will change to red. The red numbers are to remind you to refill your prescription or ask your doctor for another prescription for Albuterol Sulfate HFA. When the dose counter reaches 0, the background color will change to solid red.
- Throw the Albuterol Sulfate HFA inhaler away as soon as the dose counter says 0 or after the expiration date on the Albuterol Sulfate HFA packaging, whichever comes first. You should not keep using the inhaler after 200 sprays even though the canister may not be completely empty. You cannot be sure you will receive any medicine after using 200 sprays.
- Do not use the inhaler after the expiration date on the Albuterol Sulfate HFA packaging.

This Patient Information and Instructions for Use has been approved by the U.S. Food and Drug Administration.

Marketed by Teva Pharmaceuticals USA, Inc.
North Wales, PA 19454

Manufactured by IVAX Pharmaceuticals Ireland
Waterford, Ireland

Revised 1/2018

ASHFAIFU-002